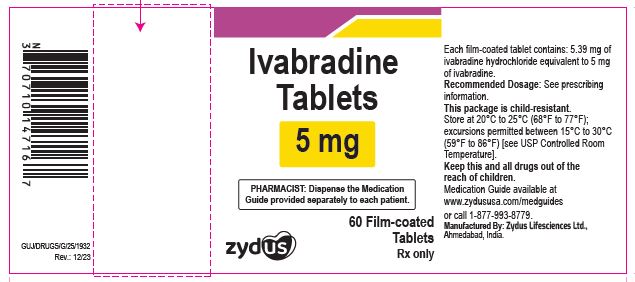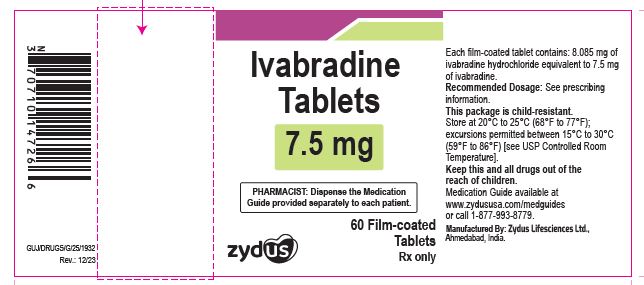 DRUG LABEL: ivabradine
NDC: 70771-1863 | Form: TABLET
Manufacturer: Zydus Lifesciences Limited
Category: prescription | Type: HUMAN PRESCRIPTION DRUG LABEL
Date: 20241130

ACTIVE INGREDIENTS: IVABRADINE HYDROCHLORIDE 5 mg/1 1
INACTIVE INGREDIENTS: ALUMINUM OXIDE; ANHYDROUS LACTOSE; D&C RED NO. 27 ALUMINUM LAKE; D&C YELLOW NO. 10; FERRIC OXIDE RED; HYPROMELLOSE 2910 (6 MPA.S); MAGNESIUM STEARATE; MICROCRYSTALLINE CELLULOSE; POLYETHYLENE GLYCOL 4000; SILICON DIOXIDE; SODIUM STARCH GLYCOLATE TYPE A POTATO; TITANIUM DIOXIDE

Ivabradine Tablets

PACKAGE LABEL.PRINCIPAL DISPLAY PANEL

Ivabradine Tablets, 5 mg

NDC 70771-1863-6

60 tablets

Rx only

Ivabradine Tablets, 5 mg

NDC 70771-1864-6

60 tablets

Rx only